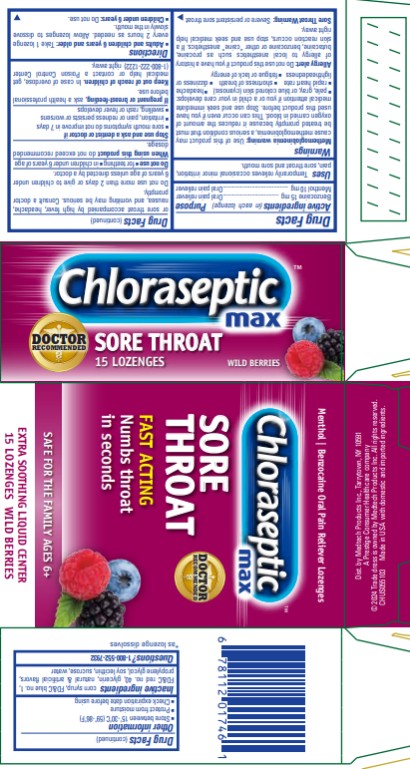 DRUG LABEL: CHLORASEPTIC MAX
NDC: 67172-114 | Form: LOZENGE
Manufacturer: Prestige Brands Holdings, Inc.
Category: otc | Type: HUMAN OTC DRUG LABEL
Date: 20250123

ACTIVE INGREDIENTS: MENTHOL 10 mg/1 1; BENZOCAINE 15 mg/1 1
INACTIVE INGREDIENTS: CORN SYRUP; FD&C BLUE NO. 1; FD&C RED NO. 40; GLYCERIN; LECITHIN, SOYBEAN; SUCROSE; WATER; PROPYLENE GLYCOL

Chloraseptic Max Lozenges - Wild Berries

Drug Facts

Active Ingredients

(in each lozenge)

Benzocaine 15 mg

Purpose

Oral pain reliever

Active Ingredients

(in each lozenge)

Menthol 10 mg

Purpose

Oral pain reliever

Uses

Temporarily relieves occasional minor irritation, pain, sore throat and sore mouth

Warnings

Methemoglobinemia warning:

Use of this product may cause methemoglobinemia, a serious condition that must be treated promptly because it reduces the amount of oxygen carried in blood. This can occur even if you have used this product before. Stop use and seek immediate medical attention if you or a child in your care develops:

∙ pale, gray, or blue colored skin (cyanosis)

∙ headache

∙ rapid heart rate

∙ shortness of breath

∙ dizziness or lightheadedness

∙ fatigue or lack of energy

Allergy Alert: Do not use this product if you have a history of allergy to local anesthetics such as procaine, butacaine, benzocaine or other “caine” anesthetics.

If a skin reaction occurs, stop use and seek medical help right away.

Sore Throat Warning: Severe or persistent sore throat or sore throat accompanied by high fever, headache, nausea and vomiting may be serious. Consult a doctor promptly. Do not use more than 2 days or give to children under 6 years of age unless directed by a doctor.

Do not use

∙ for teething

∙ in children under 6 years of age

When using this product:

do not exceed recommended dosage.

Stop use and ask a dentist or doctor if:

- sore mouth symptoms do not improve in 7 days
- irritation, pain or redness persists or worsens
- swelling, rash or fever develops

If pregnant or breast-feeding,

ask a health care professional before use.

Keep out of reach of children.

In case of overdose, get medical help or contact a Poison Control Center (1-800-222-1222) right away.

Directions

- Adults and children 6 years and older: Take 1 lozenge every 2 hours as needed. Allow lozenges to dissolve slowly in the mouth.
- Children under 6 years of age: Do not use.

Other Information

- Store between 15○ - 30○C (59○ - 86○F)
- Protect from moisture
- Check expiration date before using

Inactive Ingredients

corn syrup, FD&C blue no. 1, FD&C red no. 40, glycerin, natural & artificial flavors, propylene glycol, soy lecithin, sucrose, water

Questions?

1-800-552-7932 Chloraseptic.com

PRINCIPAL DISPLAY PANEL

Chloraseptic® Max
SORE THROAT
15 LOZENGES WILD BERRIES